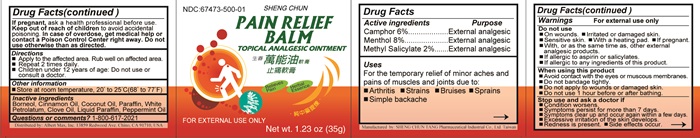 DRUG LABEL: SHENG CHUN PAIN RELIEF 
NDC: 67473-500 | Form: OINTMENT
Manufacturer: Sheng Chun Tang Pharmaceutical Industrial Co. Ltd
Category: otc | Type: HUMAN OTC DRUG LABEL
Date: 20150210

ACTIVE INGREDIENTS: CAMPHOR (NATURAL) 0.06 g/1 g; MENTHOL, UNSPECIFIED FORM 0.02 g/1 g; METHYL SALICYLATE 0.02 g/1 g
INACTIVE INGREDIENTS: BORNEOL; CINNAMON OIL; COCONUT OIL; PARAFFIN; PETROLATUM; CLOVE OIL; MINERAL OIL; PEPPERMINT OIL

Drug Facts Active ingredients

Camphor 6%
Menthol 8%
Methyl Salicylate 2%

Purpose

External analgesic

Keep out of reach of children to avoid accidental poisoning. In case of overdose, get medical help or contact a Poison Control Center right away.

Uses

For the temporary relief of minor aches and pains of muscles and joints due to:

- Arthritis
- Strains
- Bruises
- Sprains
- Simple backache

Warnings

For external use only.

Do not use

- On wounds.
- Irritated of damaged skin.
- Sensitive skin.
- With a heating pad.
- If pregnant.
- With, or as the same time as, other external analgesic products.
- If allergic to aspirin or salicylates.
- If allergic to any ingredients of this product.

When using this product

- Avoid contact with the eyes or muscous membranes.
- Do not bandage tightly.
- Do not apply to wounds or damage skin.
- Do not use 1 hour before or after bathing.

Stop use and ask a doctor if

If pregnant, ask a health professional before use.
Do not use otherwise than as directed.

- Condition worsens.
- Symptoms persist for more than 7 days.
- Symptoms clear up and occur within a few days.
- Excessive irritation of the skin develops.
- Redness is present.
- Side effects occur.

Directions

- Apply to the affected ares. Rub well on affected are.
- Repeat 2 times daily.
- Children under 12 years of age: Do not use or consult a doctor.

Other information

- Store at room temperature, 20° to 25° C (68° - 77° F)

Inactive ingredients

Borneol, Cinnamon Oil, Coconut Oil, Paraffin, White Petrolatum, Clove Oil, Liquid Paraffin, Peppermint Oil.

Questions or comments?

1-800-617-2021

PAIN RELIEF HERBAL BALM. TN Product Label

NDC: 67473-500-01

SHENG CHUN
PAIN RELIEF BALM

TOPICAL ANALGESIC OINTMENT

Relieves Pain
Herbal Essence

FOR EXTERNAL USE ONLY

Net. wt. 1.23 oz (35 g)

Distributed by: Albert Max, Inc. 13859 Redwood Avenue, Chino, CA 91710, USA

Manufactured By: SHENG CHUN TANG Pharmaceutical Industrial Co., LTD. Taiwan